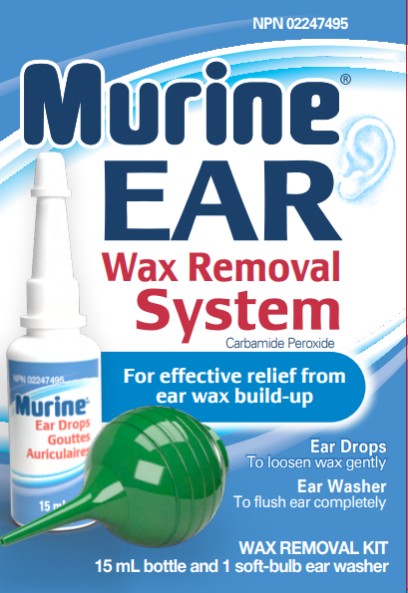 DRUG LABEL: MURINE EAR  WAX REMOVAL
NDC: 67172-362 | Form: LIQUID
Manufacturer: Prestige Brands Holdings, Inc.
Category: otc | Type: HUMAN OTC DRUG LABEL
Date: 20251030

ACTIVE INGREDIENTS: CARBAMIDE PEROXIDE 65 mg/1 mL
INACTIVE INGREDIENTS: ALCOHOL; CITRIC ACID MONOHYDRATE; GLYCERIN; POLYSORBATE 20; SODIUM CITRATE; TARTARIC ACID

Murine Ear Wax Removal System_67172-362

Drug Facts

Active ingredient

Carbamide peroxide 6.5%

Purpose

Earwax removal aid

Uses

For occasional use as an aid to soften, loosen and remove excessive ear wax

Warnings

For external use only

Do not use

this product for more than 4 days

Ask a doctor before use

- if you have ear drainage or discharge, ear pain, irritation, a rash in the ear or are dizzy
- if you have an injury or perforation (hole) of the eardrum or after ear surgery

When using this product

avoid contact with the eyes

Stop use and ask a doctor if

excessive ear wax remains after 4-day treatment with this product

Never insert cotton swabs, toothpicks, hairpins or other objects into the ear canal to remove earwax.

Keep out of reach of children.

If swallowed, get medical help or contact a Poison Control Center (1-800-222-1222) right away. If accidental contact with eyes occurs, flush eyes with water and consult a doctor.

Directions

FOR USE IN THE EAR ONLY. Remove any hearing aids before using this product.

- Adults and children over 12 years of age: tilt head sideways and place 5 to 10 drops into ear canal.

Tip of applicator should not enter ear canal.

- Keep drops in ear for several minutes by keeping head tilted or placing cotton in the ear.
- Use twice daily for up to 4 days if needed, or as directed by a doctor.
- Any wax remaining after treatment may be removed by gently flushing the ear with warm water, using a soft rubber bulb ear syringe. The tip of the ear syringe should not obstruct the flow of fluid leaving the ear.

Children under 12 years of age: consult a doctor.

Other information

- Murine® Ear Drops foam upon being placed in the ear due to the release of oxygen.
- This product is not intended to restore hearing loss due to medical reasons. In such cases, consult a doctor.
- Protect from heat and sunlight. Secure cap tightly on bottle when not in use.
- Tamper-Evident: Do not use if neckband on bottle is broken or missing.
- Check expiration date before using.

Inactive ingredients

alcohol, citric acid, glycerin, polysorbate 20, sodium citrate, tartaric acid

Questions?

1-877-854-0853

Murine.com